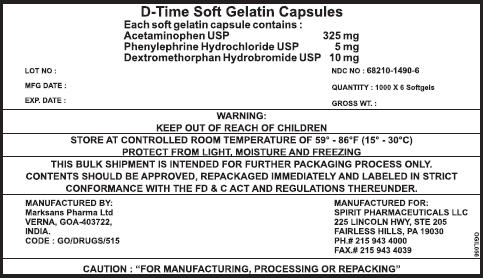 DRUG LABEL: D - TIME
NDC: 68210-1490 | Form: CAPSULE, LIQUID FILLED
Manufacturer: SPIRIT PHARMACEUTICALS,LLC
Category: otc | Type: HUMAN OTC DRUG LABEL
Date: 20100726

ACTIVE INGREDIENTS: ACETAMINOPHEN 325 mg/1 1; PHENYLEPHRINE HYDROCHLORIDE 5 mg/1 1; DEXTROMETHORPHAN HYDROBROMIDE 10 mg/1 1
INACTIVE INGREDIENTS: POLYETHYLENE GLYCOL 400; PROPYLENE GLYCOL; GELATIN; POVIDONE; SORBITOL; WATER; GLYCERIN; FD&C RED NO. 40

D-Time Soft Gelatin Capsules

Drug Facts

ACTIVE INGREDIENT

Active ingredients (in each LiquiCap) | Purpose
Acetaminophen 325mg | Pain reliever/Fever Reducer
Dextromethorphan Hbr 10mg | Cough Suppressant
Phenylephrine HCl 5 mg | Nasal Decongestant

Uses

temporarily relieves common cold/flu symptoms:

- cough due to minor throat and bronchial irritation
- sore throat
- headache
- minor aches and pains
- fever
- nasal congestion

Warnings

Alcohol Warnings :if you consume 3 or more alcoholic drinks every day, ask you doctor whether you should take acetaminophen or other pain relievers/fever reducers. Acetaminophen may cause liver damage.

Sore throat warning: If sore throat is severe, persists for more than two days, is accompanied or followed by fever,headache,rash,nausea or vomiting, consult a doctor promptly.

Do not use

- with other medicines containing acetaminophen
- if you are now taking a prescription monoamine oxidase inhibitor(MAOI) (certain drugs for depression, psychiatric or emotional conditions, or Parkinson's disease), or for 2 weeks after stopping the MAOI drug. If you do not know if your prescription drug contains an MAOI, ask a doctor or pharmacist before taking this product.

Ask a doctor before use if you have

- heart disease
- thyroid disease
- Diabetes
- high blood pressure
- trouble urinating due to enlarged postage gland
- cough that occurs with too much phlegm(mucus)
- persistent or chronic cough as occurs with smoking, asthma or emphyesma

when using this product do not use more than directed

Stop use and ask doctor if

- you get nervous,dizzy or sleepless
- symptoms get worse or last more than 5 days (children) or 7 days (adults)
- fever gets worse or less tan 3 days
- redness or swelling is present
- new symptoms occur
- cough comes back or occurs with rash or headache that lasts.

These could be signs of a serious conditions

PREGNANCY OR BREAST FEEDING

If pregnant or breast-feeding, ask a health professional before use

Keep out of reach of children.

Overdose Warning : Taking more than the recommended dose can cause serious health problems. In case of overdose,get medical help or contact a poison control center right away. Quick medical attention is critical for adults as well as for children even if you do not notice any signs or symptoms.

Direction

- take only as recommended – see Overdose warning
- do not exceed 6 doses per 24 Hours

adults and children 12 years of age and older | -2 liquicaps with water every 4 hours
children under 12 years of age | - ask a doctor

Other information

- each tablet contains : Store at room temperature

Inactive ingredients

FD &C Red No 40 IH, Polyethylene Glycol 400, Gelatin, Glycerin, Povidone, Purified water, Sorbitol

PRINCIPAL DISPLAY PANEL - 6000 Capsules Label

D-Time Soft Gelatin Capsules

Each soft gelatin capsule contains :
Acetaminophen USP | 325 mg
Phenylephrine Hydrochloride USP | 5 mg
Dextromethorphan Hydrobromide USP | 10 mg

LOT NO : | NDC NO : 68210-1490-6
MFG DATE : | QUANTITY : 1000 X 6 Softgels
EXP. DATE : | GROSS WT. :

WARNING:
KEEP OUT OF REACH OF CHILDREN

STORE AT CONTROLLED ROOM TEMPERATURE OF 59° - 86°F (15° - 30 °C)
PROTECT FROM LIGHT, MOISTURE AND FREEZING

THIS BULK SHIPMENT IS INTENDED FOR FURTHER PACKAGING PROCESS ONLY.
CONTENTS SHOULD BE APPROVED, REPACKAGED IMMEDIATELY AND LABELED IN STRICT
CONFORMANCE WITH THE FD & C ACT AND REGULATIONS THEREUNDER.

MANUFACTURED BY:
Marksans Pharma Ltd
VERNA, GOA-403722,
INDIA.
CODE : GO/DRUGS/515

MANUFACTURED FOR:
SPIRIT PHARMACEUTICALS LLC
225 LINCOLN HWY, STE 205
FAIRLESS HILLS, PA 19030
PH.# 215 943 4000
FAX.# 215 943 4039

CAUTION : "FOR MANUFACTURING, PROCESSING OR REPACKING"

OGIL056